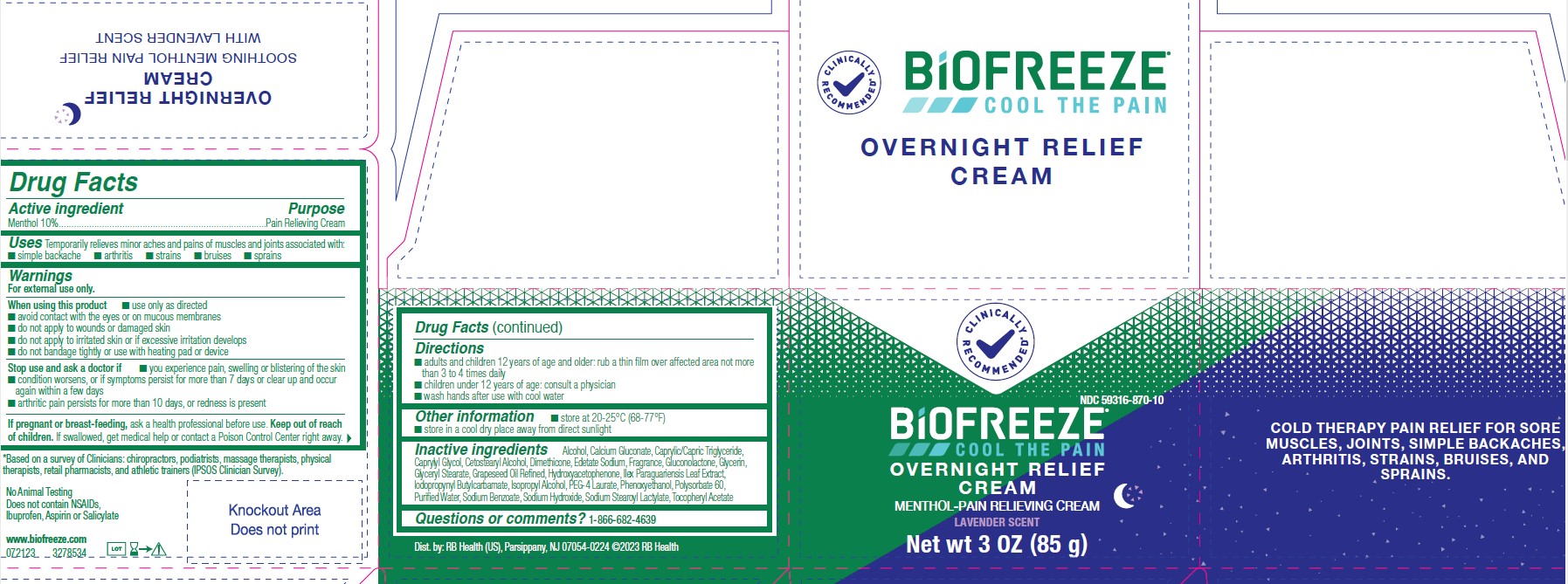 DRUG LABEL: Biofreeze
NDC: 59316-870 | Form: CREAM
Manufacturer: RB Health (US) LLC
Category: otc | Type: HUMAN OTC DRUG LABEL
Date: 20240202

ACTIVE INGREDIENTS: MENTHOL, UNSPECIFIED FORM 100 mg/1 g
INACTIVE INGREDIENTS: ALCOHOL; CETOSTEARYL ALCOHOL; ISOPROPYL ALCOHOL; PEG-4 LAURATE; GLYCERIN; CALCIUM GLUCONATE; MEDIUM-CHAIN TRIGLYCERIDES; CAPRYLYL GLYCOL; DIMETHICONE; GLUCONOLACTONE; GLYCERYL MONOSTEARATE; HYDROXYACETOPHENONE; ILEX PARAGUARIENSIS LEAF; IODOPROPYNYL BUTYLCARBAMATE; PHENOXYETHANOL; POLYSORBATE 60; SODIUM BENZOATE; SODIUM HYDROXIDE; SODIUM STEAROYL LACTYLATE; EDETATE SODIUM; .ALPHA.-TOCOPHEROL ACETATE; GRAPE SEED OIL; WATER

Biofreeze Overnight Relief Cream

Active Ingredients:

Menthol USP 10%

Purpose

Cooling Pain Relief

Uses:

Temporary relief from minor aches and pains of sore muscles and joints associated with: • arthritis • backache • strains • sprains •bruises

Warnings:

For external use only

When using this product:

■ use only as directed
■ avoid contact with the eyes or on mucous membranes
■ do not apply to wounds or damaged skin
■ do not apply to irritated skin or if excessive irritation develops
■ do not bandage tightly or use with heating pad or device

Stop use and ask a doctor if:

Condition worsens, or if symptoms persist for more than 7 days, or clear up and recur

If pregnant or breastfeeding:

Ask a health professional before use

Keep out of reach of children:

If accidentally ingested, get medical help or contact a Poison Control Center immediately

Directions:

■ adults and children 12 years of age and older: rub a thin film over affected area not more
than 3 to 4 times daily
■ children under 12 years of age: consult a physician

■ wash hands after use with cool water

Inactive Ingredients:

Alcohol, Calcium Gluconate, Caprylic/Capric Triglyceride,
Caprylyl Glycol, Cetostearyl Alcohol, Dimethicone, Edetate Sodium, Fragrance, Gluconolactone, Glycerin,
Glyceryl Stearate, Grapeseed Oil Refined, Hydroxyacetophenone, Ilex Paraguariensis Leaf Extract,
Iodopropynyl Butylcarbamate, Isopropyl Alcohol, PEG-4 Laurate, Phenoxyethanol, Polysorbate 60,
PurifiedWater, Sodium Benzoate, Sodium Hydroxide, Sodium Stearoyl Lactylate, Tocopheryl Acetate

Questions or Comments:

1-800-246-3733